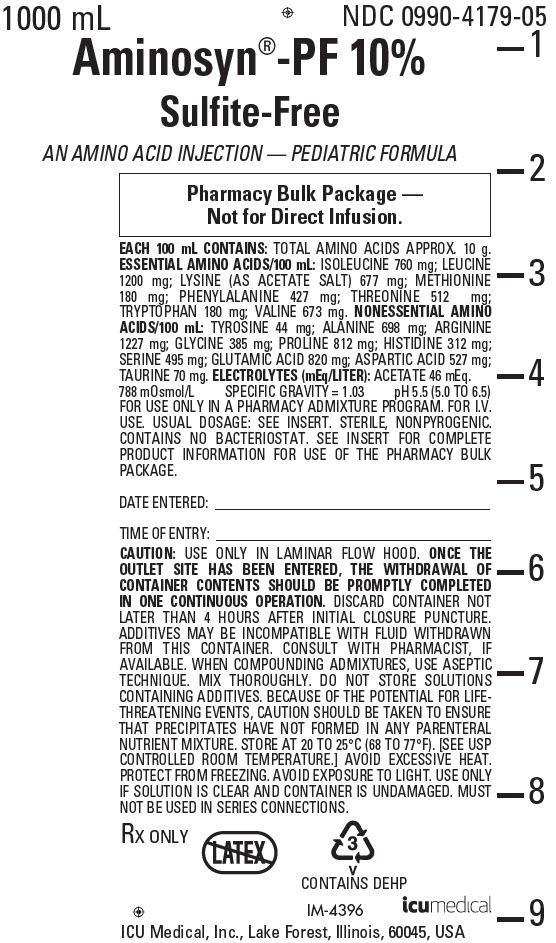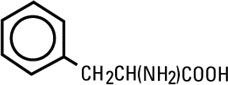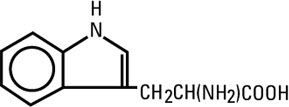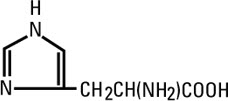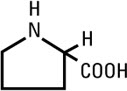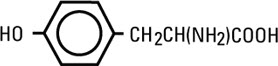 DRUG LABEL: Aminosyn-PF
NDC: 0990-4179 | Form: INJECTION, SOLUTION
Manufacturer: ICU Medical Inc.
Category: prescription | Type: HUMAN PRESCRIPTION DRUG LABEL
Date: 20251010

ACTIVE INGREDIENTS: ISOLEUCINE 760 mg/100 mL; LEUCINE 1200 mg/100 mL; LYSINE ACETATE 677 mg/100 mL; METHIONINE 180 mg/100 mL; PHENYLALANINE 427 mg/100 mL; THREONINE 512 mg/100 mL; TRYPTOPHAN 180 mg/100 mL; VALINE 673 mg/100 mL; ALANINE 698 mg/100 mL; ARGININE 1227 mg/100 mL; ASPARTIC ACID 527 mg/100 mL; GLUTAMIC ACID 820 mg/100 mL; GLYCINE 385 mg/100 mL; HISTIDINE 312 mg/100 mL; PROLINE 812 mg/100 mL; SERINE 495 mg/100 mL; TAURINE 70 mg/100 mL; TYROSINE 44 mg/100 mL
INACTIVE INGREDIENTS: WATER

Aminosyn® -PF 10%
Sulfite-Free

AN AMINO ACID INJECTION - PEDIATRIC FORMULA

Pharmacy Bulk Package − Not for Direct Infusion.

Flexible Plastic Container

Rx only

DESCRIPTION

Aminosyn®-PF 10%, Sulfite-Free, (an amino acid injection — pediatric formula) is a sterile, nonpyrogenic solution for intravenous infusion. Aminosyn-PF 10% is oxygen sensitive. The Pharmacy Bulk Package is a sterile dosage form which contains multiple single doses for use only in a pharmacy bulk admixture program. The formulation is described below:

Aminosyn-PF 10%
An Amino Acid Injection — Pediatric Formula
Essential Amino Acids (mg/100 mL)
Isoleucine | 760
Leucine | 1200
Lysine (acetate)* | 677
Methionine | 180
Phenylalanine | 427
Threonine | 512
Tryptophan | 180
Valine | 673
* Amount cited is for lysine alone and does not include the acetate salt.

Nonessential Amino Acids (mg/100 mL)
Alanine | 698
Arginine | 1227
Aspartic Acid | 527
Glutamic Acid | 820
Glycine | 385
Histidine | 312
Proline | 812
Serine | 495
Taurine | 70
Tyrosine | 44

Electrolytes (mEq/L)
Sodium (Na^+) | None
Potassium (K^+) | None
Chloride (Cl^−) | None
Acetate (C2H3O2^−) a | 46

Product Characteristics
Protein Equivalent (Approx. grams/L) | 100
Total Nitrogen (grams/L) | 15.2
Osmolarity (mOsmol/L) | 788
pH (range) | 5.5 (5.0 to 6.5)
Specific Gravity | 1.03
a From lysine acetate.

The formulas for the individual amino acids present in Aminosyn-PF 10% are as follows:

Essential Amino Acids
Isoleucine | CH3CH2CH(CH3)CH(NH2)COOH
Leucine | (CH3)2CHCH2CH(NH2)COOH
Lysine Acetate | H2N(CH2)4CH(NH2)COOH • CH3COOH
Methionine | CH3S(CH2)2CH(NH2)COOH
Phenylalanine
Threonine | CH3CH(OH)CH(NH2)COOH
Tryptophan
Valine | (CH3)2CHCH(NH2)COOH

Nonessential Amino Acids
Alanine | CH3CH(NH2)COOH
Arginine | H2NC(NH)NH(CH2)3CH(NH2)COOH
L-Aspartic Acid | HOOCCH2CH(NH2)COOH
L-Glutamic Acid | HOOC(CH2)2CH(NH2)COOH
Glycine | H2NCH2COOH
Histidine
Proline
Serine | HOCH2CH(NH2)COOH
Taurine | H2N − CH2CH2− SO3H
Tyrosine

The flexible plastic container is fabricated from a specially formulated polyvinylchloride. Water can permeate from inside the container into the overwrap but not in amounts sufficient to affect the solution significantly.

Solutions in contact with the plastic container may leach out certain chemical components from the plastic in very small amounts; however, biological testing was supportive of the safety of the plastic container materials.

Exposure to temperatures above 25°C/77°F during transport and storage will lead to minor losses in moisture content. Higher temperatures lead to greater losses. It is unlikely that these minor losses will lead to clinically significant changes within the expiration period.

The Pharmacy Bulk Package is designed for use with manual, gravity flow operations and automated compounding devices for preparing sterile parenteral nutrient admixtures; it contains no bacteriostat. Multiple single doses may be dispensed during continual aliquoting operations. Withdrawal of container contents should be promptly completed within 4 hours after initial closure puncture.

CLINICAL PHARMACOLOGY

Aminosyn-PF 10%, Sulfite-Free, (an amino acid injection — pediatric formula) contains a mixture of essential and nonessential amino acids as well as taurine. The amino acid composition has been specifically formulated to provide a well-tolerated nitrogen source for nutritional support and therapy for infants and young children. When administered in conjunction with a cysteine hydrochloride additive, Aminosyn-PF 10% results in plasma amino acid concentrations approximating a profile consistent with that of a breast-fed infant.

The rationale for Aminosyn-PF 10% is based on the observation of inadequate levels of essential amino acids in the plasma of infants receiving total parenteral nutrition (TPN) using conventional amino acid solutions.

Clinical studies in infants who required TPN therapy showed that infusion of Aminosyn-PF 10% resulted in plasma amino acid concentrations approximating those of normal breast or formula fed infants. In addition, weight gains, nitrogen balance, and serum protein concentrations were consistent with an improving nutritional status.

When infused with hypertonic dextrose as a calorie source, supplemented with cysteine hydrochloride, electrolytes, vitamins, and minerals, Aminosyn-PF 10% provides TPN for infants and young children, with the exception of essential fatty acids.

It is thought that the acetate from lysine acetate under the conditions of parenteral nutrition, does not impact net acid-base balance when renal and respiratory functions are normal. Clinical evidence seems to support this thinking; however, confirmatory experimental evidence is not available. The amounts of sodium and acetate in Aminosyn-PF 10% are not of clinical significance.

The addition of a cysteine hydrochloride additive will contribute to the chloride load.

The electrolyte content of any additives that are introduced should be carefully considered and included in input computations.

The human newborn conjugates bile with taurine which becomes the primary method of biliary excretion. Taurine deficiency because of its effect on bile salt conjugation and, therefore, on bile salt flow may be of major importance in the genesis of cholestasis. Taurine has also been shown to play a role in central nervous system development.

INDICATIONS AND USAGE

Aminosyn-PF 10%, Sulfite-Free, (an amino acid injection — pediatric formula) is indicated for the nutritional support of infants (including those of low birth weight) and young children requiring TPN via either central or peripheral infusion routes. Parenteral nutrition with Aminosyn-PF 10% is indicated to prevent nitrogen and weight loss or treat negative nitrogen balance in infants and young children where (1) the alimentary tract by the oral gastrostomy, or jejunostomy route, cannot or should not be used or adequate protein intake is not feasible by these routes; (2) gastrointestinal absorption of protein is impaired; or (3) protein requirements are substantially increased as with extensive burns. Dosage, route of administration, and concomitant infusion of non-protein calories are dependent on various factors, such as nutritional and metabolic status of the patient, anticipated duration of parenteral nutrition support, and vein tolerance. See DOSAGE AND ADMINISTRATION for additional information.

Central Venous Infusion

Central venous infusion should be considered when amino acid solutions are to be admixed with hypertonic dextrose to promote protein synthesis in hypercatabolic or severely depleted infants or those requiring long-term parenteral nutrition.

Peripheral Parenteral Nutrition

For moderately catabolic or depleted patients in whom the central venous route is not indicated, diluted amino acid solutions mixed with 5 to 10% dextrose solutions may be infused by peripheral vein, supplemented, if desired, with fat emulsion.

CONTRAINDICATIONS

Aminosyn-PF 10%, Sulfite-Free, (an amino acid injection — pediatric formula) is contraindicated in patients with untreated anuria, hepatic coma, inborn errors of amino acid metabolism (including those involving branched chain amino acid metabolism such as maple syrup urine disease and isovaleric acidemia), or hypersensitivity to one or more amino acids present in the solution.

WARNINGS

Safe, effective use of parenteral nutrition requires a knowledge of nutrition as well as clinical expertise in recognition and treatment of the complications which can occur. FREQUENT EVALUATION AND LABORATORY DETERMINATIONS ARE NECESSARY FOR PROPER MONITORING OF PARENTERAL NUTRITION. Studies should include blood sugar, serum proteins, kidney and liver function tests, electrolytes, hemogram, carbon dioxide content, serum osmolalities, blood cultures, and blood ammonia levels.

Administration of amino acids in the presence of impaired renal function or gastrointestinal bleeding may augment an already elevated blood urea nitrogen. Patients with azotemia from any cause should not be infused with amino acids without regard to total nitrogen intake.

Administration of intravenous solutions can cause fluid and/or solute overload resulting in dilution of serum electrolyte concentrations, overhydration, congested states, or pulmonary edema. The risk of dilutional states is inversely proportional to the electrolyte concentrations of the solutions.

Administration of amino acid solutions to a patient with hepatic insufficiency may result in plasma amino acid imbalances, hyperammonemia, prerenal azotemia, stupor and coma.

Hyperammonemia is of special significance in infants, as its occurrence in the syndrome caused by genetic metabolic defects is sometimes associated, although not necessarily in a causal relationship, with mental retardation. This reaction appears to be dose-related and is more likely to develop during prolonged therapy. It is essential that blood ammonia levels be measured frequently in infants.

Conservative doses of amino acids should be given, dictated by the nutritional status of the patient. Should symptoms of hyperammonemia develop, amino acid dosage levels should be reduced and titrated against serum ammonia levels.

WARNING: This product contains aluminum that may be toxic. Aluminum may reach toxic levels with prolonged parenteral administration if kidney function is impaired. Premature neonates are particularly at risk because their kidneys are immature, and they require large amounts of calcium and phosphate solutions, which contain aluminum.

Research indicates that patients with impaired kidney function, including premature neonates, who receive parenteral levels of aluminum at greater than 4 to 5 mcg/kg/day accumulate aluminum at levels associated with central nervous system and bone toxicity. Tissue loading may occur at even lower rates of administration.

PRECAUTIONS

Clinical evaluation and periodic laboratory determinations are necessary to monitor changes in fluid balance, electrolyte concentrations, and acid-base balance during prolonged parenteral therapy or whenever the condition of the patient warrants such evaluation. Significant deviations from normal concentrations may require the use of additional electrolyte supplements.

Strongly hypertonic nutrient solutions should be administered via an intravenous catheter placed in a central vein, preferably the superior vena cava.

Care should be taken to avoid circulatory overload, particularly in patients with cardiac insufficiency.

Special care must be taken when giving hypertonic dextrose to a diabetic or pre-diabetic patient. To prevent severe hyperglycemia in such patients, insulin may be required.

Administration of glucose at a rate exceeding the patient’s utilization rate may lead to hyperglycemia, coma, and death.

The effect of infusion of amino acids, without dextrose, upon carbohydrate metabolism of children is not known at this time. It is essential to provide adequate exogenous dextrose calories concurrently with amino acids. Administration of amino acids without carbohydrates may result in the accumulation of ketone bodies in the blood. Correction of this ketonemia may be achieved by the administration of carbohydrate.

Essential fatty acid deficiency (EFAD) is becoming increasingly recognized in patients on long term TPN (more than 5 days). The use of fat emulsion to provide 4 — 10% of total caloric intake as linoleic acid may prevent EFAD.

Peripheral administration of Aminosyn-PF 10%, Sulfite-Free, (an amino acid injection — pediatric formula) requires appropriate dilution and provision of adequate calories. Care should be taken to assure proper placement of the needle within the lumen of the vein. The venipuncture site should be inspected frequently for signs of infiltration. If venous thrombosis or phlebitis occurs, discontinue infusion or change infusion site and initiate appropriate treatment.

Extraordinary electrolyte losses such as may occur during protracted nasogastric suction, vomiting, diarrhea, or gastrointestinal fistula drainage may necessitate additional electrolyte supplementation.

Metabolic acidosis can be prevented or readily controlled by adding a portion of the cations in the electrolyte mixture as acetate salts and in the case of hyperchloremic acidosis, by keeping the total chloride content of the infusate to a minimum.

Aminosyn-PF 10% contains no chloride.

Aminosyn-PF 10% contains no added phosphorus. Patients, especially those with hypophosphatemia, may require the addition of phosphate. To prevent hypocalcemia, calcium supplementation should always accompany phosphate administration. To assure adequate intake, serum levels should be monitored frequently.

Aminosyn-PF 10% contains no more than 25 mcg/L of aluminum.

To minimize the risk of possible incompatibilities arising from mixing this solution with other additives that may be prescribed, the final infusate should be inspected for cloudiness or precipitation immediately after mixing, prior to administration, and periodically during administration.

BOXED WARNING

SPECIAL PRECAUTIONS FOR

CENTRAL INFUSIONS

ADMINISTRATION BY CENTRAL VENOUS CATHETER SHOULD BE

USED ONLY BY THOSE FAMILIAR WITH THIS TECHNIQUE

AND ITS COMPLICATIONS.

Central vein infusion (with added concentrated carbohydrate solutions) of amino acid solutions requires a knowledge of nutrition as well as clinical expertise in recognition and treatment of complications. Attention must be given to solution preparation, administration and patient monitoring. IT IS ESSENTIAL THAT A CAREFULLY PREPARED PROTOCOL, BASED ON CURRENT MEDICAL PRACTICES, BE FOLLOWED, PREFERABLY BY AN EXPERIENCED TEAM.

SUMMARY HIGHLIGHTS OF COMPLICATIONS (See also Current Medical Literature).

1. Technical
  The placement of a central venous catheter should be regarded as a surgical procedure. One should be fully acquainted with various techniques of catheter insertion. For details of technique and placement sites, consult the medical literature. X-ray is the best means of verifying catheter placement. Complications known to occur from the placement of central venous catheters are pneumothorax, hemothorax, hydrothorax, artery puncture and transection, injury to the brachial plexus, malposition of the catheter, formation of arteriovenous fistula, phlebitis, thrombosis and air and catheter emboli.
2. Septic
  The constant risk of sepsis is present during administration of total parenteral nutrition. It is imperative that the preparation of the solution and the placement and care of catheters be accomplished under strict aseptic conditions.
  Solutions should ideally be prepared in the hospital pharmacy under a laminar flow hood using careful aseptic technique to avoid inadvertent touch contamination. Solutions should be used promptly after mixing. Storage should be under refrigeration and limited to a brief period of time, preferably less than 24 hours.
  Administration time for a single container and set should never exceed 24 hours.
3. Metabolic
  The following metabolic complications have been reported with TPN administration: Metabolic acidosis and alkalosis, hypophosphatemia, hypocalcemia, osteoporosis, hyperglycemia and glycosuria, rebound hypoglycemia, osmotic diuresis and dehydration, elevated liver enzymes, hypo- and hypervitaminosis, electrolyte imbalances and hyperammonemia in children. Frequent evaluations are necessary especially during the first few days of therapy to prevent or minimize these complications.
  Administration of glucose at a rate exceeding the patient’s utilization rate may lead to hyperglycemia, coma and death. CLINICAL EVALUATION AND LABORATORY DETERMINATIONS, AT THE DISCRETION OF THE ATTENDING PHYSICIAN ARE NECESSARY FOR PROPER MONITORING DURING ADMINISTRATION. Do not withdraw venous blood for blood chemistries through the peripheral infusion site, as interference with estimations of nitrogen-containing substances may occur. Blood studies should include glucose, urea nitrogen, serum electrolytes, ammonia, cholesterol, acid-base balance, serum proteins, kidney and liver function tests, osmolarity and hemogram. White blood count and blood cultures are to be determined if indicated. Urinary osmolality and glucose should be determined as necessary.

Pregnancy Category C

Animal reproduction studies have not been conducted with Aminosyn-PF 10%. It is also not known whether Aminosyn-PF 10% can cause fetal harm when administered to a pregnant woman or can affect reproduction capacity. Aminosyn-PF 10% should be given to a pregnant woman only if clearly needed.

ADVERSE REACTIONS

Local reactions consisting of erythema, phlebitis and thrombosis at the infusion site have occurred with peripheral intravenous infusion of amino acids particularly if other substances, such as antibiotics, are also administered through the same site. In such cases the infusion site should be changed promptly to another vein. Use of large peripheral veins, inline filters, and slowing the rate of infusion may reduce the incidence of local venous irritation. Electrolyte additives should be spread throughout the day. Irritating additive medications may need to be injected at another venous site.

Generalized flushing, fever and nausea also have been reported during peripheral infusions of amino acid solutions.

If an adverse reaction does occur, discontinue the infusion, evaluate the patient, institute appropriate therapeutic countermeasures and save the remainder of the fluid for examination if deemed necessary.

OVERDOSAGE

In the event of overhydration or solute overload, re-evaluate the patient and institute appropriate corrective measures. See WARNINGS and PRECAUTIONS.

DOSAGE AND ADMINISTRATION

Aminosyn-PF 10%, Sulfite-Free, is an amino acid injection-pediatric formula not intended for direct infusion. Admixtures should be made by or under the direction of a pharmacist using strict aseptic technique under a laminar flow hood. Admixtures must be stored under refrigeration and used within 24 hours of admixing.

The total daily dose of the solution depends on the daily protein requirements and on the patient’s metabolic and clinical response.

Pediatric requirements for parenteral nutrition are constrained by the greater relative fluid requirements of the infant and greater caloric requirements per kilogram than in the adult.

The recommended intravenous dose of Aminosyn-PF 10% is up to 2.5 g amino acid/kg/day for infants up to 10 kg. For infants and children larger than 10 kg, the total daily dose of amino acids should be up to 25 g amino acids/day for the first 10 kg of body weight plus 1.0 to 1.25 g amino acid for each kg of body weight over 10 kg. Initial amino acid dosage levels of 1.0 g/kg/day may be increased gradually in increments of 0.5 g/kg/day to approximate desired intake levels.

Aminosyn-PF 10% should be diluted with dextrose prior to use. Nonprotein calories should constitute approximately 100 to 130 kcal/kg/day. Part of the nonprotein caloric requirement may be provided as lipid emulsion administered concurrently to provide up to 60% of daily calories at a dose not to exceed 4 g fat/kg/day. Fluid intake for the infant receiving central venous TPN should be approximately 125 mL/kg/day (range: 100 to 175 mL/kg/day), depending on the clinical condition of the patient. Fat emulsion coadministration should be considered when prolonged (more than 5 days) parenteral nutrition is required in order to prevent essential fatty acid deficiency (EFAD). Serum lipids should be monitored for evidence of EFAD in patients maintained on fat-free TPN. Premature infants with respiratory distress syndrome suspected of having a patent ductus arteriosus should be given fluids more cautiously.

Cysteine is considered to be an essential amino acid for infants, especially preterm infants with potentially immature enzyme pathways. Therefore, addition of a cysteine supplement to the TPN admixture is recommended. The intake of cysteine by the preterm infant ingesting maternal milk is approximately 78 mg/kg/day. The suggested intravenous dosage level for Cysteine Hydrochloride Injection, USP is 500 mg (10 mL) for every 12.5 g (125 mL) of Aminosyn-PF 10% administered (see package insert for Cysteine Hydrochloride Injection, USP). In order to avoid potential insolubility of cysteine hydrochloride in admixtures, the foregoing concentration should not be exceeded.

In many patients, provision of adequate calories in the form of hypertonic dextrose may require the administration of exogenous insulin to prevent hyperglycemia and glycosuria. To prevent rebound hypoglycemia, a solution containing 5% dextrose should be administered when hypertonic dextrose solutions are abruptly discontinued.

SERUM ELECTROLYTES SHOULD BE MONITORED FREQUENTLY. Electrolytes may be added to the nutrient solution as indicated by the patient’s clinical condition and laboratory determinations of plasma values. Major electrolytes are sodium, chloride, potassium, phosphate, magnesium and calcium. Daily administration of intravenous vitamin supplements including a complete complement of fat and water-soluble vitamins is required. Trace metal additives including zinc, copper, manganese, and chromium should also be provided, especially when long-term parenteral therapy is anticipated.

Calcium and phosphorus are added to the solution as indicated.

Potentially incompatible ions such as calcium and phosphate may be added to alternate infusate bottles to avoid precipitation. In patients with hyperchloremic or other metabolic acidosis, sodium and potassium may be added as the acetate or lactate salts to provide bicarbonate alternates. Bicarbonate should not be administered during infusion of the nutritional solution unless deemed absolutely necessary.

Additives may be incompatible. Consult with pharmacist, if available. When introducing additives, use aseptic technique, mix thoroughly and do not store.

To ensure the precise delivery of the small volumes of fluid necessary for total parenteral nutrition in infants, accurately calibrated and reliable infusion systems should be used.

Central Venous Nutrition

Hypertonic mixtures of amino acids and dextrose may be safely administered by continuous infusion through a central venous catheter with the tip located in the superior vena cava. Initial infusion rates should be slow, and gradually increased to the recommended 60-125 mL per kilogram body weight per day. If administration rate should fall behind schedule, no attempt to “catch up” to planned intake should be made. In addition to meeting protein needs, the rate of administration, particularly during the first few days of therapy, is governed by the patient’s glucose tolerance. Daily intake of amino acids and dextrose should be increased gradually to the maximum required dose as indicated by frequent determinations of glucose levels in blood and urine.

Peripheral Parenteral Nutrition

For patients in whom the central venous route is not indicated and who can consume adequate calories enterally, Aminosyn-PF 10% may be administered by peripheral vein with parenteral nonprotein calories. The concentration of dextrose in the final admixture is 5 to 10%, and simultaneous administration of lipid emulsion is recommended both as a calorie source and to attenuate the potentially irritating effects of the hypertonic nutritional admixture. Fat emulsion may comprise up to 60% of the daily caloric intake at a dosage level not to exceed 4 g fat/kg/day. It is essential that peripheral infusion be accompanied by adequate caloric intake.

Parenteral drug products should be inspected visually for particulate matter and discoloration prior to administration, whenever solution and container permit. COLOR VARIATION FROM PALE YELLOW TO YELLOW IS NORMAL AND DOES NOT ALTER EFFICACY.

Recommended Directions for Use of the Pharmacy Bulk Package

Use Aseptic Technique

1. During use, container must be stored, and all manipulations performed, in an appropriate laminar flow hood.
2. Remove cover from outlet port at bottom of container.
3. Insert piercing pin of sterile transfer set and suspend unit in a laminar flow hood. Insertion of a piercing pin into the outlet port should be performed only once in a Pharmacy Bulk Package solution. Once the outlet site has been entered, the withdrawal of container contents should be completed promptly in one continuous operation. Should this not be possible, a maximum time of 4 hours from transfer set pin or implement insertion is permitted to complete fluid transfer operations; i.e., discard container no later than 4 hours after initial closure puncture.
4. Sequentially dispense aliquots of Aminosyn-PF 10% into I.V. containers using appropriate transfer set. During fluid transfer operations, the Pharmacy Bulk Package should be maintained under the storage conditions recommended in the labeling.
  Additives may be incompatible with fluid withdrawn from this container. Consult with pharmacist, if available. When compounding admixtures, use aseptic technique. Mix thoroughly. Do not store solutions containing additives. Because of the potential for life-threatening events, caution should be taken to ensure that precipitates have not formed in any parenteral nutrient mixture.

WARNING: Do not use flexible container in series connections.

HOW SUPPLIED

Aminosyn -PF 10%, Sulfite-Free, (an amino acid injection — pediatric formula) is supplied as a Pharmacy Bulk Package in 1000 mL flexible plastic containers NDC 0409-4179-05 / NDC 0990-4179-05.

ICU Medical is transitioning NDC codes from the "0409" to a "0990" labeler code. Both NDC codes are expected to be in the market for a period of time.

Store at 20 to 25°C (68 TO 77°F). [See USP Controlled Room Temperature.] Protect from freezing. Avoid exposure to light.

Revised: August, 2018

EN-4678

ICU Medical, Inc., Lake Forest, Illinois, 60045, USA

PRINCIPAL DISPLAY PANEL - 1000 mL Bag Label

1000 mL
NDC 0990-4179-05

Aminosyn®-PF 10%

Sulfite-Free

AN AMINO ACID INJECTION — PEDIATRIC FORMULA

Pharmacy Bulk Package —
Not for Direct Infusion.

EACH 100 mL CONTAINS: TOTAL AMINO ACIDS APPROX. 10 g.
ESSENTIAL AMINO ACIDS/100 mL: ISOLEUCINE 760 mg; LEUCINE
1200 mg; LYSINE (AS ACETATE SALT) 677 mg; METHIONINE
180 mg; PHENYLALANINE 427 mg; THREONINE 512 mg;
TRYPTOPHAN 180 mg; VALINE 673 mg. NONESSENTIAL AMINO
ACIDS/100 mL: TYROSINE 44 mg; ALANINE 698 mg; ARGININE
1227 mg; GLYCINE 385 mg; PROLINE 812 mg; HISTIDINE 312 mg;
SERINE 495 mg; GLUTAMIC ACID 820 mg; ASPARTIC ACID 527 mg;
TAURINE 70 mg. ELECTROLYTES (mEq/LITER): ACETATE 46 mEq.
788 mOsmol/L SPECIFIC GRAVITY = 1.03 pH 5.5 (5.0 TO 6.5)
FOR USE ONLY IN A PHARMACY ADMIXTURE PROGRAM. FOR I.V.
USE. USUAL DOSAGE: SEE INSERT. STERILE, NONPYROGENIC.
CONTAINS NO BACTERIOSTAT. SEE INSERT FOR COMPLETE
PRODUCT INFORMATION FOR USE OF THE PHARMACY BULK
PACKAGE.

DATE ENTERED:

TIME OF ENTRY:

CAUTION: USE ONLY IN LAMINAR FLOW HOOD. ONCE THE
OUTLET SITE HAS BEEN ENTERED, THE WITHDRAWAL OF
CONTAINER CONTENTS SHOULD BE PROMPTLY COMPLETED
IN ONE CONTINUOUS OPERATION. DISCARD CONTAINER NOT
LATER THAN 4 HOURS AFTER INITIAL CLOSURE PUNCTURE.
ADDITIVES MAY BE INCOMPATIBLE WITH FLUID WITHDRAWN
FROM THIS CONTAINER. CONSULT WITH PHARMACIST, IF
AVAILABLE. WHEN COMPOUNDING ADMIXTURES, USE ASEPTIC
TECHNIQUE. MIX THOROUGHLY. DO NOT STORE SOLUTIONS
CONTAINING ADDITIVES. BECAUSE OF THE POTENTIAL FOR LIFE-
THREATENING EVENTS, CAUTION SHOULD BE TAKEN TO ENSURE
THAT PRECIPITATES HAVE NOT FORMED IN ANY PARENTERAL
NUTRIENT MIXTURE. STORE AT 20 TO 25°C (68 TO 77°F). [SEE USP
CONTROLLED ROOM TEMPERATURE.] AVOID EXCESSIVE HEAT.
PROTECT FROM FREEZING. AVOID EXPOSURE TO LIGHT. USE ONLY
IF SOLUTION IS CLEAR AND CONTAINER IS UNDAMAGED. MUST
NOT BE USED IN SERIES CONNECTIONS.

Rx ONLY

3
v
CONTAINS DEHP

IM-4396
icumedical

ICU Medical, Inc., Lake Forest, Illinois, 60045, USA